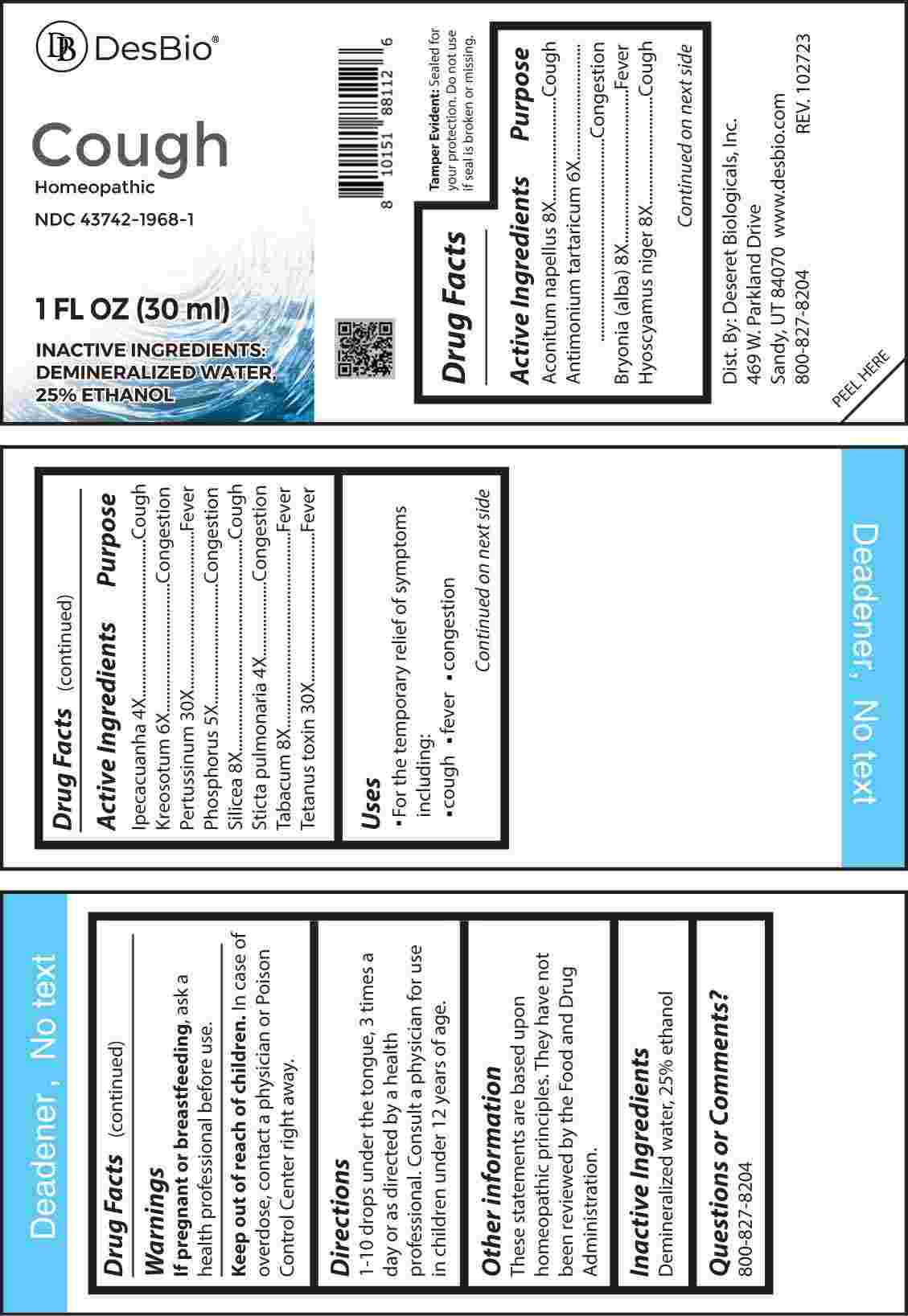 DRUG LABEL: Cough
NDC: 43742-1968 | Form: LIQUID
Manufacturer: Deseret Biologicals, Inc.
Category: homeopathic | Type: HUMAN OTC DRUG LABEL
Date: 20240219

ACTIVE INGREDIENTS: IPECAC 4 [hp_X]/1 mL; LOBARIA PULMONARIA 4 [hp_X]/1 mL; PHOSPHORUS 5 [hp_X]/1 mL; ANTIMONY POTASSIUM TARTRATE 6 [hp_X]/1 mL; WOOD CREOSOTE 6 [hp_X]/1 mL; ACONITUM NAPELLUS WHOLE 8 [hp_X]/1 mL; BRYONIA ALBA ROOT 8 [hp_X]/1 mL; HYOSCYAMUS NIGER 8 [hp_X]/1 mL; SILICON DIOXIDE 8 [hp_X]/1 mL; TOBACCO LEAF 8 [hp_X]/1 mL; HUMAN SPUTUM, BORDETELLA PERTUSSIS INFECTED 30 [hp_X]/1 mL; TETANUS TOXIN 30 [hp_X]/1 mL
INACTIVE INGREDIENTS: WATER; ALCOHOL

DRUG FACTS:

ACTIVE INGREDIENTS:

Aconitum Napellus 8X, Antimonium Tartaricum 6X, Bryonia (Alba) 8X, Hyoscyamus Niger 8X, Ipecacuanha 4X, Kreosotum 6X, Pertussinum 30X, Phosphorus 5X, Silicea 8X, Sticta Pulmonaria 4X, Tabacum 8X, Tetanus Toxin 30X.

PURPOSE:

Aconitum Napellus - Cough, Antimonium Tartaricum - Congestion, Bryonia (Alba) - Fever, Hyoscyamus Niger - Cough, Ipecacuanha - Cough, Kreosotum - Congestion, Pertussinum - Fever, Phosphorus - Congestion, Silicea - Cough, Sticta Pulmonaria - Congestion, Tabacum - Fever, Tetanus Toxin - Fever

USES:

• For the temporary relief of symptoms including:

• cough • fever • congestion

These statements are based upon homeopathic principles. They have not been reviewed by the Food and Drug Administration.

WARNINGS:

If pregnant or breast-feeding, ask a health professional before use.

Keep out of reach of children. In case of overdose, contact a physician or Poison Control Center right away.

Tamper Evident: Sealed for your protection.

Do not use if seal is broken or missing.

KEEP OUT OF REACH OF CHILDREN:

In case of overdose, contact a physician or Poison Control Center right away.

DIRECTIONS:

1-10 drops under the tongue, 3 times a day or as directed by a health professional. Consult a physician for use in children under 12 years of age.

INACTIVE INGREDIENTS:

Demineralized water, 25% ethanol

QUESTIONS:

Dist. By: Deseret Biologicals, Inc.
469 W. Parkland Drive
Sandy, UT 84070

www.desbio.com

800-827-8204

PACKAGE LABEL DISPLAY:

DesBio

Cough

Homeopathic
NDC 43742-1968-1
1 FL OZ (30 ml)